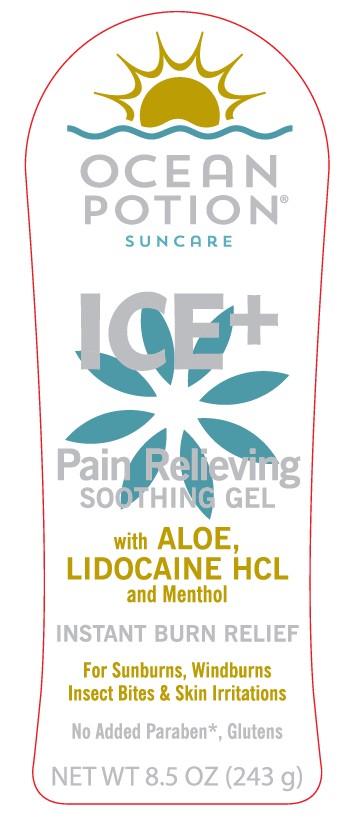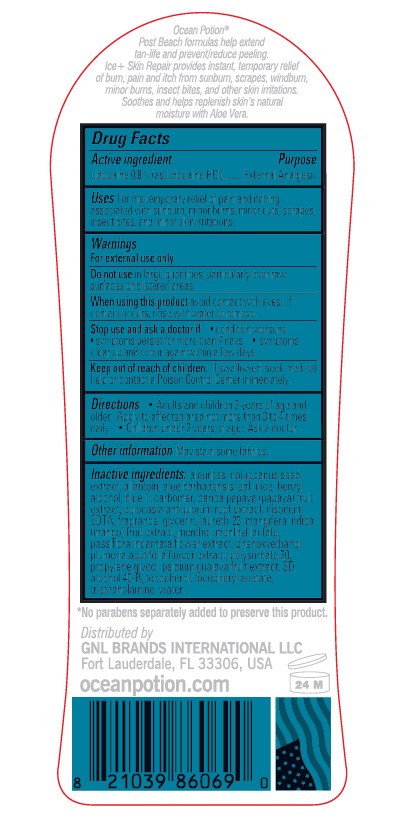 DRUG LABEL: Ocean Potion Suncare Ice Plus Pain Relieving Soothing
NDC: 85638-005 | Form: GEL
Manufacturer: GNL BRANDS INTERNATIONAL, LLC
Category: otc | Type: HUMAN OTC DRUG LABEL
Date: 20250815

ACTIVE INGREDIENTS: LIDOCAINE HYDROCHLORIDE 8 mg/1 g
INACTIVE INGREDIENTS: MANGO; ALCOHOL; PROPYLENE GLYCOL; LAURETH-23; GLYCERIN; POLYSORBATE 20; ALLANTOIN; CARBOMER INTERPOLYMER TYPE A (ALLYL SUCROSE CROSSLINKED); TROLAMINE; MENTHYL LACTATE, (-)-; EDETATE DISODIUM; LEVOMENTHOL; KUKUI NUT OIL; PAPAYA; COLOCASIA ESCULENTA ROOT; PASSIFLORA INCARNATA FLOWER; GUAVA; .ALPHA.-TOCOPHEROL ACETATE; .ALPHA.-TOCOPHEROL, DL-; FD&C BLUE NO. 1; ALOE VERA LEAF; WATER; PLUMERIA ALBA FLOWER OIL; BENZYL ALCOHOL; PHENOXYETHANOL

Ocean Potion Suncare Ice Plus Pain Relieving Soothing Gel

Active ingredient

Lidocaine 0.8% (as Lidocaine HCI)

Purpose

External Analgesic

Uses

For the temporary relief of pain and itching associated with sunburn, minor burns, minor cuts, scrapes, insect bites, and minor skin irritations

Warnings

For External Use Only

Do not use

in large quantities, particularly over raw surfaces or blistered areas

When using this product

avoid contact with eyes. If contact occurs, rinse with water to remove.

Stop use and ask a doctor if

• condition worsens • symptoms persist for more than 7 days • symptoms clear up and occur again within a few days

Keep out of reach of children

If swallowed, seek medical help or contact a Poison Control Center immediately.

Directions

• Adults and children 2 years of age and older: Apply to affected area not more than 3 to 4 times daily

• Children under 2 years of age: Ask a doctor.

Inactive ingredients

aleurites moluccanus seed extract, allantoin, aloe barbadensis leaf juice, benzyl alcohol, blue 1, carbomer, carica papaya (papaya) fruit extract, colocasia antiquorum root extract, disodium EDTA, fragrance, glycerin, laureth-23, mangifera indica (mango) fruit extract, menthol, menthyl lactate, passiflora incarnata flower extract, phenoxyethanol, plumeria acutifolia flower extract, polysorbate 20, propylene glycol, psidium guajava fruit extract, SD alcohol 40-B, tocopherol, tocopheryl acetate (vitamin e), triethanolamine, water.